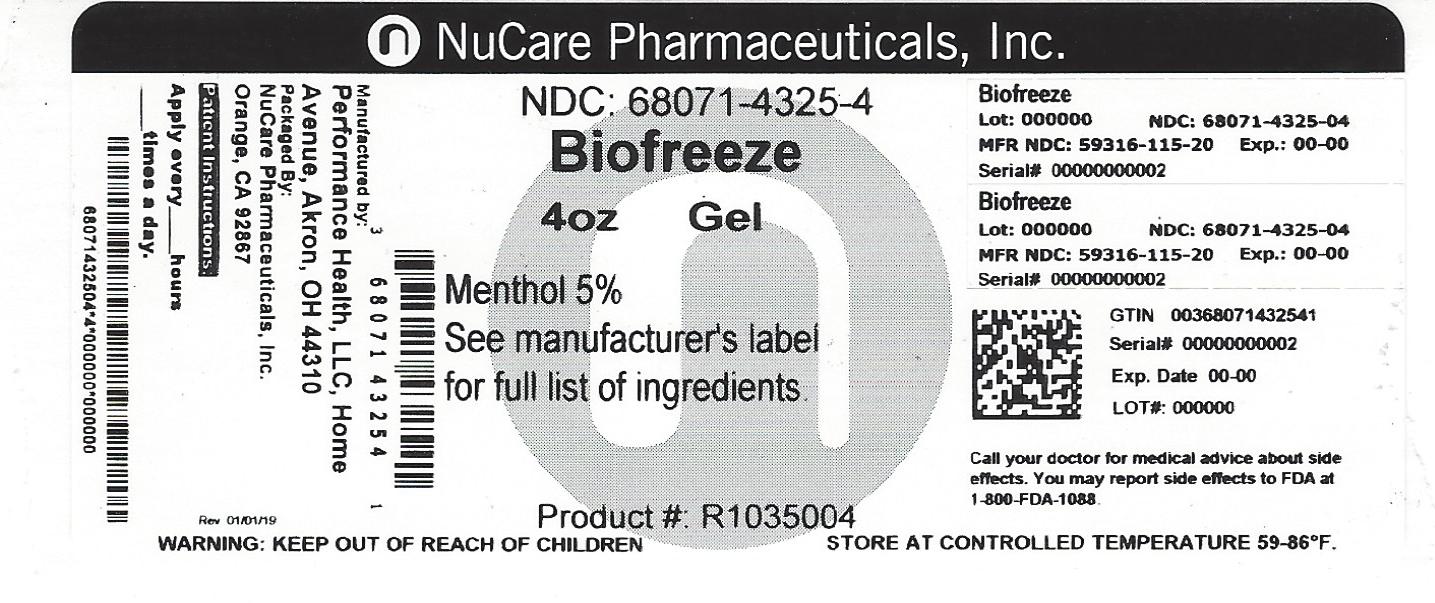 DRUG LABEL: Biofreeze Professional
NDC: 68071-4325 | Form: GEL
Manufacturer: NuCare Pharmaceuticals,Inc.
Category: otc | Type: HUMAN OTC DRUG LABEL
Date: 20240606

ACTIVE INGREDIENTS: MENTHOL, UNSPECIFIED FORM 50 mg/1 mL
INACTIVE INGREDIENTS: ALOE VERA LEAF; ARCTIUM LAPPA ROOT; ARNICA MONTANA FLOWER; FD&C BLUE NO. 1; FRANKINCENSE; CALENDULA OFFICINALIS FLOWER; GREEN TEA LEAF; CARBOXYPOLYMETHYLENE; GLYCERIN; ILEX PARAGUARIENSIS LEAF; ISOPROPYL ALCOHOL; ISOPROPYL MYRISTATE; MELISSA OFFICINALIS LEAF; SILICON DIOXIDE; .ALPHA.-TOCOPHEROL ACETATE; TROLAMINE; WATER; FD&C YELLOW NO. 5

Biofreeze Professional Gel

Active Ingredients:

Menthol USP 5%

Purpose

Cooling Pain Relief

Uses:

Temporary relief from minor aches and pains of sore muscles and joints associated with arthiritis, backache, strains and sprains

Warnings:

For external use only

Flammable: Keep away from excessive heat or open flame

Ask a doctor before use if you have:

Sensitive skin

When using this product:

Avoid contact with the eyes or mucous membranes; Do not apply to wounds or damaged skin; Do not use with other ointments, creams, sprays or liniment; Do not apply to irritated skin or if excessive irritation develops; Do not bandage; Wash hands after use with cool water; Do not use with heating pad or device; Store in cool dry place

Stop use and ask a doctor If:

Condition worsens, or if symptoms persist for more than 7 days , or clear up and recur

If pregnant or breast-feeding:

Ask a health professional before use

Keep out of reach of children:

If accidentally ingested, get medical help or contact a Poison Control Center immediately

Directions:

Adults and Children 2 years of age and older: Rub a thin film over affected areas not more four times daily; massage not necessary Children under 2 years of age: Consult physician

Inactive Ingredients:

Aloe Barbadensis Leaf Extract, Arctium Lappa Root (Burdock) Extract, Arnica Montana Flower Extract, Blue 1, Boswellia Carterii Resin Extract, Calendula Officinalis Extract, Camellia Sinensis Leaf Extract, Carbomer, Glycerin, Ilex Paraguariensis Leaf Extract, Isopropyl Alcohol, Isopropyl Myristate, Melissa Officinalis (Lemon Balm) Leaf Extract, Silica, Tocopheryl Acetate, Triethanolamine, Water, Yellow 5

Questions or Comments:

1-800-246-3733